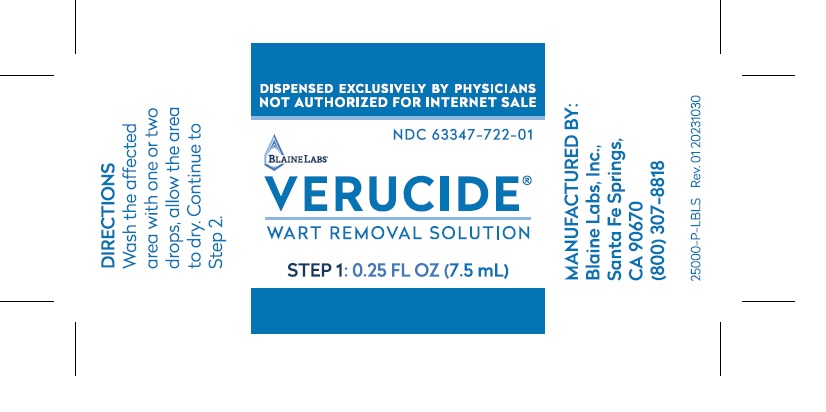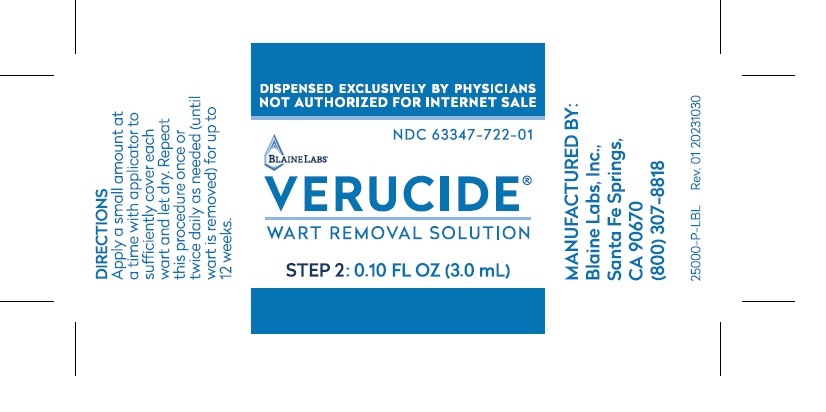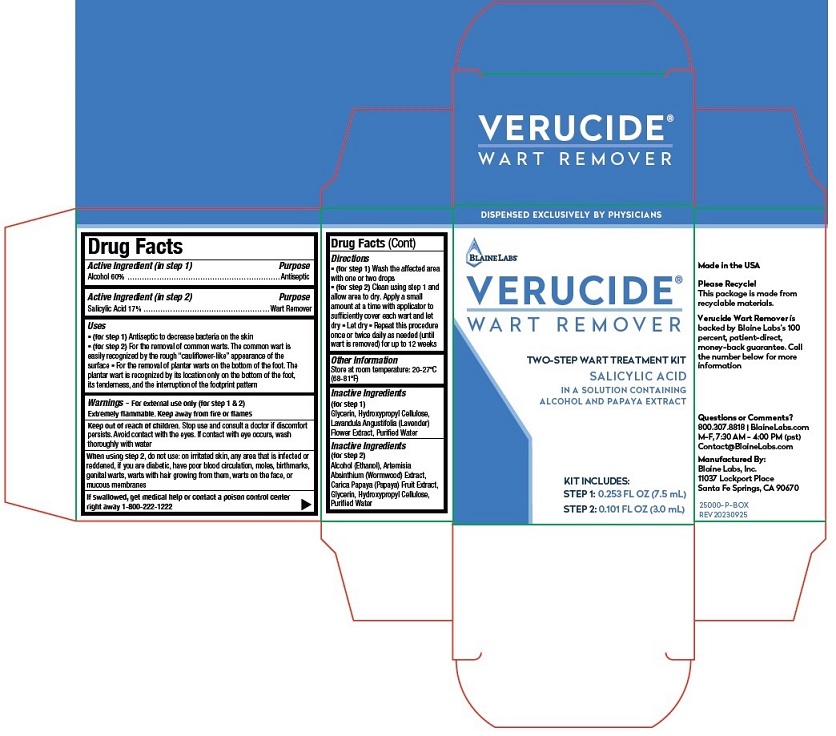 DRUG LABEL: VERUCIDE WART REMOVER Kit
NDC: 63347-720 | Form: KIT | Route: TOPICAL
Manufacturer: Blaine Labs Inc.
Category: otc | Type: HUMAN OTC DRUG LABEL
Date: 20250102

ACTIVE INGREDIENTS: ALCOHOL 60 g/100 mL; SALICYLIC ACID 17 g/100 mL
INACTIVE INGREDIENTS: GLYCERIN; HYDROXYPROPYL CELLULOSE, UNSPECIFIED; LAVANDULA ANGUSTIFOLIA SUBSP. ANGUSTIFOLIA FLOWER; WATER; ALCOHOL; WORMWOOD; PAPAYA; GLYCERIN; HYDROXYPROPYL CELLULOSE, UNSPECIFIED; WATER

VERUCIDE®Wart Remover Kit

Drug Facts

Active Ingredient (in step 1)...................... Alcohol 60%

Active Ingredient (in step 2) ............. Salicylic Acid 17%

Purpose

Alcohol 60% (step 1) ............................................................... Antiseptic

Salicylic Acid 17% (step 2) ................................................ Wart Remover

Uses
■ (for step 1)Antiseptic to decrease bacteria on the skin
■ (for step 2)For the removal of common warts. The common wart is
easily recognized by the rough “cauliflower-like” appearance of the
surface ■ For the removal of plantar warts on the bottom of the foot. The
plantar wart is recognized by its location only on the bottom of the foot,
its tenderness, and the interruption of the footprint pattern

WARNINGS

Warnings- For external use only (for step 1 & 2)
Extremely flammable. Keep away from fire or flames

Keep out of reach of children.Stop use and consult a doctor if discomfort
persists. Avoid contact with the eyes. If contact with eye occurs, wash
thoroughly with water

WHEN USING

When using step 2, do not use: on irritated skin, any area that is infected or
reddened, if you are diabetic, have poor blood circulation, moles, birthmarks,
genital warts, warts with hair growing from them, warts on the face, or
mucous membranes

If swallowed, get medical help or contact a poison control center
right away 1-800-222-1222

Directions

■ (for step 1)Wash the affected area
with one or two drops
■ (for step 2)Clean using step 1 and
allow area to dry. Apply a small
amount at a time with applicator to
sufficiently cover each wart and let
dry ■ Let dry ■ Repeat this procedure
once or twice daily as needed (until
wart is removed) for up to 12 weeks

Other Information

Store at room temperature: 20-27ºC
(68-81ºF)

Inactive Ingredients

(for step 1)
Glycerin, Hydroxypropyl Cellulose,
Lavandula Angustifolia (Lavender)
Flower Extract, Purified Water

(for step 2)
Alcohol (Ethanol), Artemisia
Absinthium (Wormwood) Extract,
Carica Papaya (Papaya) Fruit Extract,
Glycerin, Hydroxypropyl Cellulose,
Purified Water

Questions or Comments?
800.307.8818 | BlaineLabs.com
M-F, 7:30 AM - 4:00 PM (pst)
Contact@BlaineLabs.com

VERUCIDE®Wart Remover Kit Labeling

BLAINE LABS ` NDC 63347-720-01

VERUCIDE ®
WART REMOVER

TWO-STEP WART TREATMENT KIT

SALICYLIC ACID
IN A SOLUTION CONTAINING
ALCOHOL AND PAPAYA EXTRACT

KIT INCLUDES:
STEP 1: 0.253 FL OZ (7.5 mL)
STEP 2: 0.101 FL OZ (3.0 mL)

Manufactured By:
Blaine Labs, Inc.
11037 Lockport Place
Santa Fe Springs, CA 90670

Step1

Step2

res